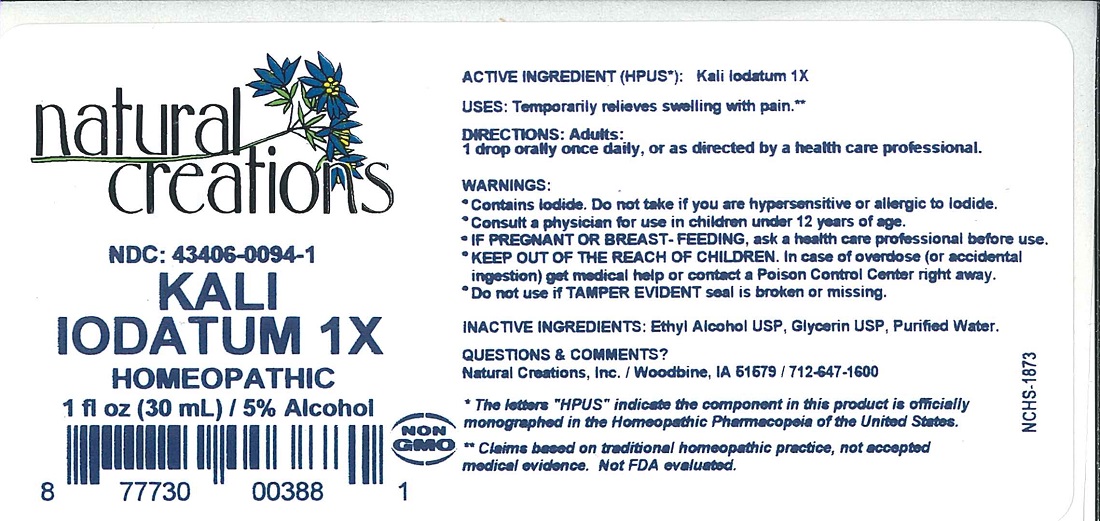 DRUG LABEL: KALI IODATUM 1X
NDC: 43406-0094 | Form: LIQUID
Manufacturer: Natural Creations, Inc.
Category: homeopathic | Type: HUMAN OTC DRUG LABEL
Date: 20251216

ACTIVE INGREDIENTS: POTASSIUM IODIDE 1 [hp_X]/1 mL
INACTIVE INGREDIENTS: ALCOHOL; WATER

KALI IODATUM 1X

Active Ingredient (HPUS*): Kali Iodatum 1X

PURPOSE

Uses: Temporarily relieves swelling with pain.**

INDICATIONS AND USAGE

Uses: Temporarily relieves swelling with pain.**

DOSAGE AND ADMINISTRATION

Directions: Adults & children above 12 years: 1 drop orally once daily, or as directed by a health care professional.

WARNINGS:

- Consult a physician for use in children under 12 years of age.
- IF PREGNANT OR BREAST-FEEDING, ask a health care professional before use.
- KEEP OUT OF THE REACH OF CHILDREN. In case of overdose (or accidental ingestion) get medical help or contact a Poison Control Center right away.
- Do not use if TAMPER EVIDENT seal is broken or missing.

WARNINGS:

*Consult a physician for use in children under 12 years of age.

* IF PREGNANT OR BREAST-FEEDING, ask a health care professional before use.

* KEEP OUT OF THE REACH OF CHILDREN. In case of overdose (or accidental ingestion) get medical help or contact a Poison Control Center right away.

INACTIVE INGREDIENT

Inactive Ingredients: Ethyl Alcohol USP, Glycerin USP, Purified Water.

Questions & Comments?

Natural Creations, Inc. / Woodbine, IA 51579 / 712-647-1600

REFERENCES

* The letters "HPUS" indicate the component in this product is officially monographed in the Homeopathic Pharmacopeia of the United States.

**Claims based on traditional homeopathic practice, not accepted medical evidence. Not FDA evaluated.

PACKAGE LABEL

NDC: 43406-0094-1

KALI IODATUM 1X

HOMEOPATHIC

1 fl oz (30 mL) 5% Alcohol

UPC: 877730003881